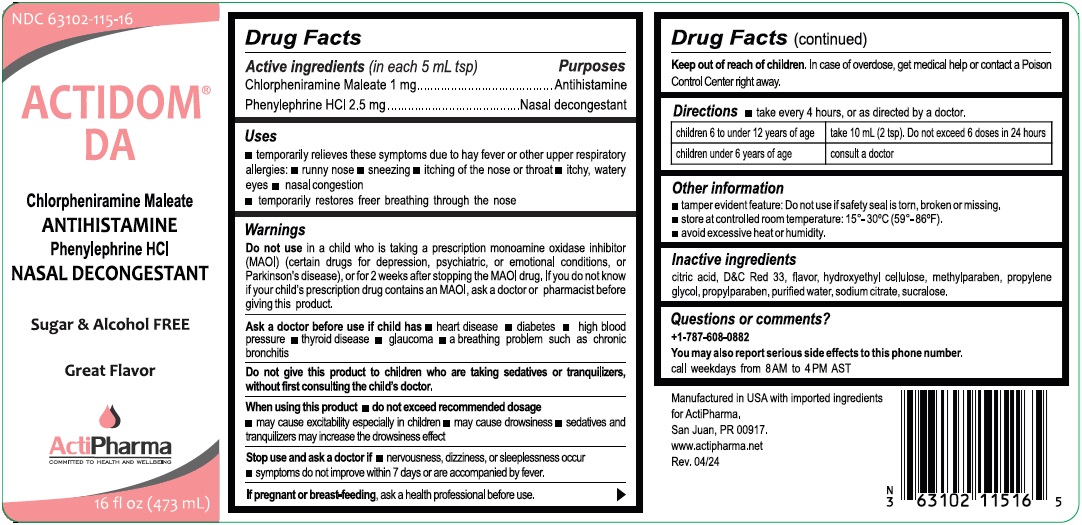 DRUG LABEL: ACTIDOM DA
NDC: 63102-115 | Form: SOLUTION
Manufacturer: ACTIPHARMA, LLC
Category: otc | Type: HUMAN OTC DRUG LABEL
Date: 20240715

ACTIVE INGREDIENTS: CHLORPHENIRAMINE MALEATE 1 mg/5 mL; PHENYLEPHRINE HYDROCHLORIDE 2.5 mg/5 mL
INACTIVE INGREDIENTS: CITRIC ACID MONOHYDRATE; D&C RED NO. 33; HYDROXYETHYL CELLULOSE, UNSPECIFIED; METHYLPARABEN; PROPYLENE GLYCOL; PROPYLPARABEN; WATER; SODIUM CITRATE, UNSPECIFIED FORM; SUCRALOSE

ACTIDOM® DA

Active ingredients (in each 5 mL tsp)

Chlorpheniramine Maleate 1 mg
Phenylephrine HCL 2.5 mg

Purposes

Antihistamine
Nasal decongestant

Uses

• temporarily relieves these symptoms due to hay fever or other upper respiratory allergies: • runny nose • sneezing • itching of the nose or throat
• itchy, watery eyes • nasal congestion
• temporarily restores free breathing through the nose

Warnings

Do not use in a child who is taking a prescription monoamine oxidase inhibitor (MAOI) (certain drugs for depression, psychiatric, or emotional conditions, or Parkinson's disease), or for 2 weeks after stopping the MAOI drug. If you do not know if your child's prescription drug contains an MAOI, ask a doctor or pharmacist before giving this product.

Ask a doctor before use if child has • heart disease • diabetes • high blood pressure • thyroid disease • glaucoma • a breathing problem such as chronic bronchitis

Do not give this product to children who are taking sedatives or tranquilizers, without first consulting the child's doctor.

When using this product • do not exceed recommended dosage
• may cause excitability especially in children • may cause drowsiness • sedatives and tranquilizers may increase the drowsiness effect

Stop use and ask a doctor if • nervousness, dizziness, or sleeplessness occur
• symptoms do not improve within 7 days or are accompanied by fever.

If pregnant or breast-feeding, ask a health professional before use.

Keep out of reach of children. In case of overdose, get medical help or contact a Poison Control Center right away.

Directions

take every 4 hours, or as directed by a doctor.

children 6 to under 12 years of age | take 10 mL (2 tsp). Do not exceed 6 doses in 24 hours
children under 6 years of age | consult a doctor

Other information

• tamper evident feature: Do not use if safety seal is torn, broken or missing.
• store at controlled room temperature: 15°-30°C (59°-86°F).
• avoid excessive heat or humidity.

Inactive ingredients

citric acid, D&C Red 33, flavor, hydroxyethyl cellulose, methylparaben, propylene glycol, propylparaben, purified water, sodium citrate, sucralose.

Questions or comments?

+1-787-608-0882
You may also report serious side effects to this phone number.
call weekdays from 8AM to 4 PM AST

Sugar & Alcohol FREE

Great Flavor

Manufactured in USA with imported ingredients
for ActiPharma.
San Juan, PR 00917.
www.actipharma.net